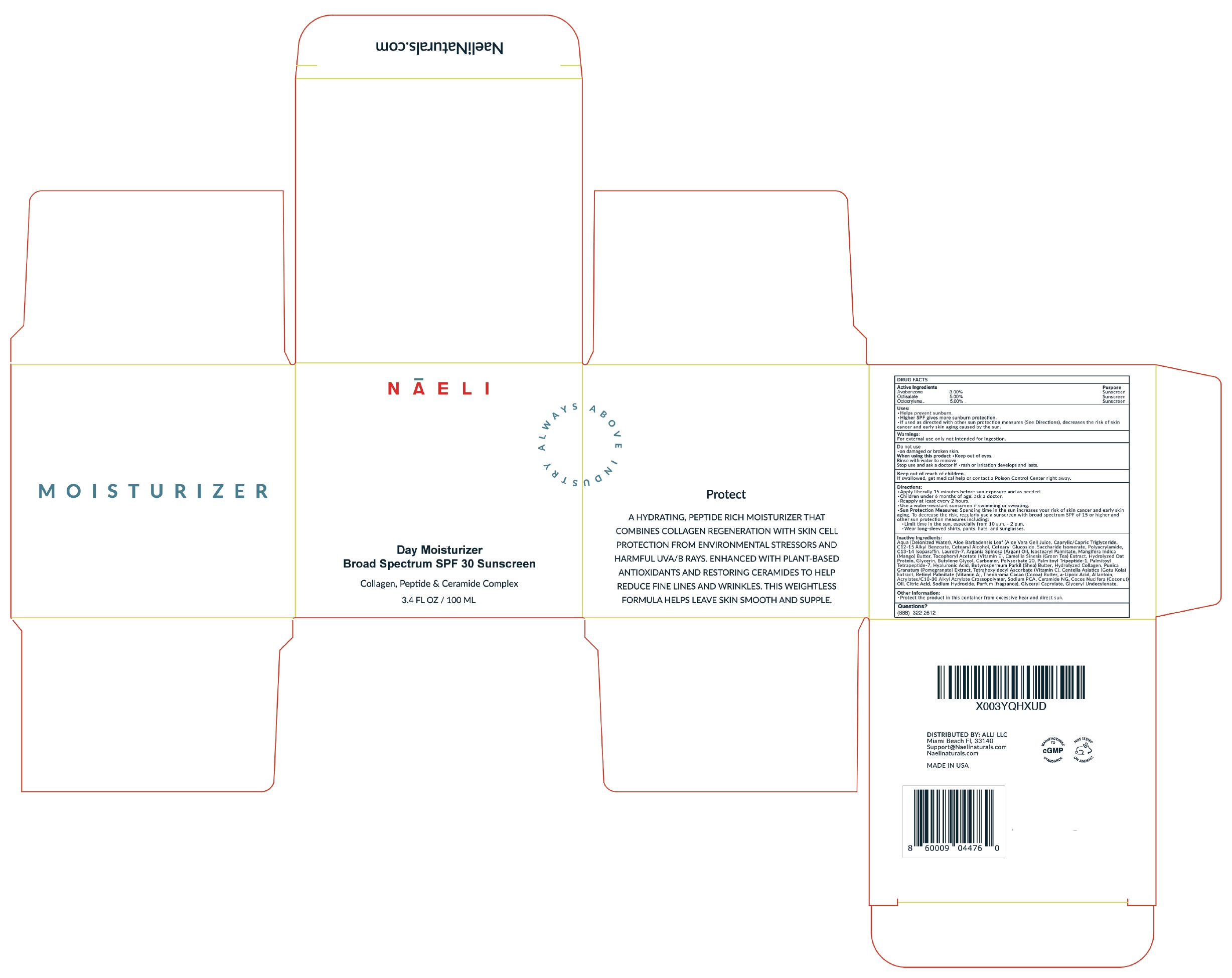 DRUG LABEL: NAELI Day Moisturizer Broad Spectrum SPF 30
NDC: 73670-649 | Form: CREAM
Manufacturer: ALLI LLC
Category: otc | Type: HUMAN OTC DRUG LABEL
Date: 20240606

ACTIVE INGREDIENTS: AVOBENZONE 30 mg/1 mL; OCTISALATE 50 mg/1 mL; OCTOCRYLENE 50 mg/1 mL
INACTIVE INGREDIENTS: WATER; ALOE VERA LEAF; MEDIUM-CHAIN TRIGLYCERIDES; ALKYL (C12-15) BENZOATE; CETOSTEARYL ALCOHOL; CETEARYL GLUCOSIDE; SACCHARIDE ISOMERATE; C13-14 ISOPARAFFIN; LAURETH-7; ARGAN OIL; ISOSTEARYL PALMITATE; .ALPHA.-TOCOPHEROL ACETATE; GREEN TEA LEAF; GLYCERIN; BUTYLENE GLYCOL; POLYSORBATE 20; PALMITOYL TRIPEPTIDE-1; PALMITOYL TETRAPEPTIDE-7; HYALURONIC ACID; SHEA BUTTER; PUNICA GRANATUM ROOT BARK; TETRAHEXYLDECYL ASCORBATE; CENTELLA ASIATICA TRITERPENOIDS; VITAMIN A PALMITATE; ALLANTOIN; SODIUM PYRROLIDONE CARBOXYLATE; CERAMIDE NG; COCONUT OIL; CITRIC ACID MONOHYDRATE; SODIUM HYDROXIDE; GLYCERYL CAPRYLATE

NAELI Day Moisturizer Broad Spectrum SPF-30

Active Ingredients

Avobenzone 3.00%

Octisalate 5.00%

Octocrylene 5.00%

Purpose

Sunscreen

Uses:

- Helps prevent sunburn.
- Higher SPF gives more sunburn protection.
- If used as directed with other sun protection measures (See Directions), decreases the risk of skin cancer and early skin aging caused by the sun.

Warnings:

For external use only not intended for ingestion.

Do not use

- on damaged or broken skin.

When using this product

- Keep out of eyes.

Rinse with water to remove

Stop use and ask a doctor if

- rash or irritation develops and lasts.

Keep out of reach of children.

If swallowed, get medical help or contact a Poison Control Center right away.

Directions:

- Apply liberally 15 minutes before sun exposure and as needed.
- Children under 6 months of age: ask a doctor.
- Reapply at least every 2 hours
- Use a water-resistant sunscreen if swimming or sweating.
- Sun Protection Measures:Spending time in the sun increases your risk of skin cancer and early skin aging. To decrease the risk, regularly use a sunscreen with broad spectrum SPF of 15 or higher and other sun protection measures including:
- Limit time in the sun, especially from 10 a.m. - 2 p.m.
- Wear long-sleeved shirts, pants, hats, and sunglasses.

Inactive Ingredients:

Aqua (Deionized Water), Aloe Barbadensis Leaf (Aloe Vera Gel) Juice, Caprylic/Capric Triglyceride, C12-15 Alkyl Benzoate, Cetearyl Alcohol, Cetearyl Glucoside, Saccharide Isomerate, Polyacrylamide, C13-14 Isoparaffin, Laureth-7, Argania Spinosa (Argan) Oil, Isostearyl Palmitate, Mangifera Indica (Mango) Butter, Tocopheryl Acetate (Vitamin E), Camellia Sinesis (Green Tea) Extract, Hydrolyzed Oat Protein, Glycerin, Butylene Glycol, Carbomer, Polysorbate 20, Palmitoyl Tripeptide-1, Palmitoyl Tetrapeptide-7, Hyaluronic Acid, Butyrospermum Parkii (Shea) Butter, Hydrolyzed Collagen, Punica Granatum (Pomegranate) Extract, Tetrahexyldecyl Ascorbate (Vitamin C), Centella Asiatica (Gotu Kola) Extract, Retinyl Palmitate (Vitamin A), Theobroma Cacao (Cocoa) Butter, a-Lipoic Acid, Allantoin, Acrylates/C10-30 Alkyl Acrylate Crossopolymer, Sodium PCA, Ceramide NG, Cocos Nucifera (Coconut) Oil, Citric Acid, Sodium Hydroxide, Parfum (fragrance), Glyceryl Caprylate, Glyceryl Undecylenate.

Other Information:

- Protect the product in this container from excessive heat and direct sun.

Questions?

(888) 322-2612